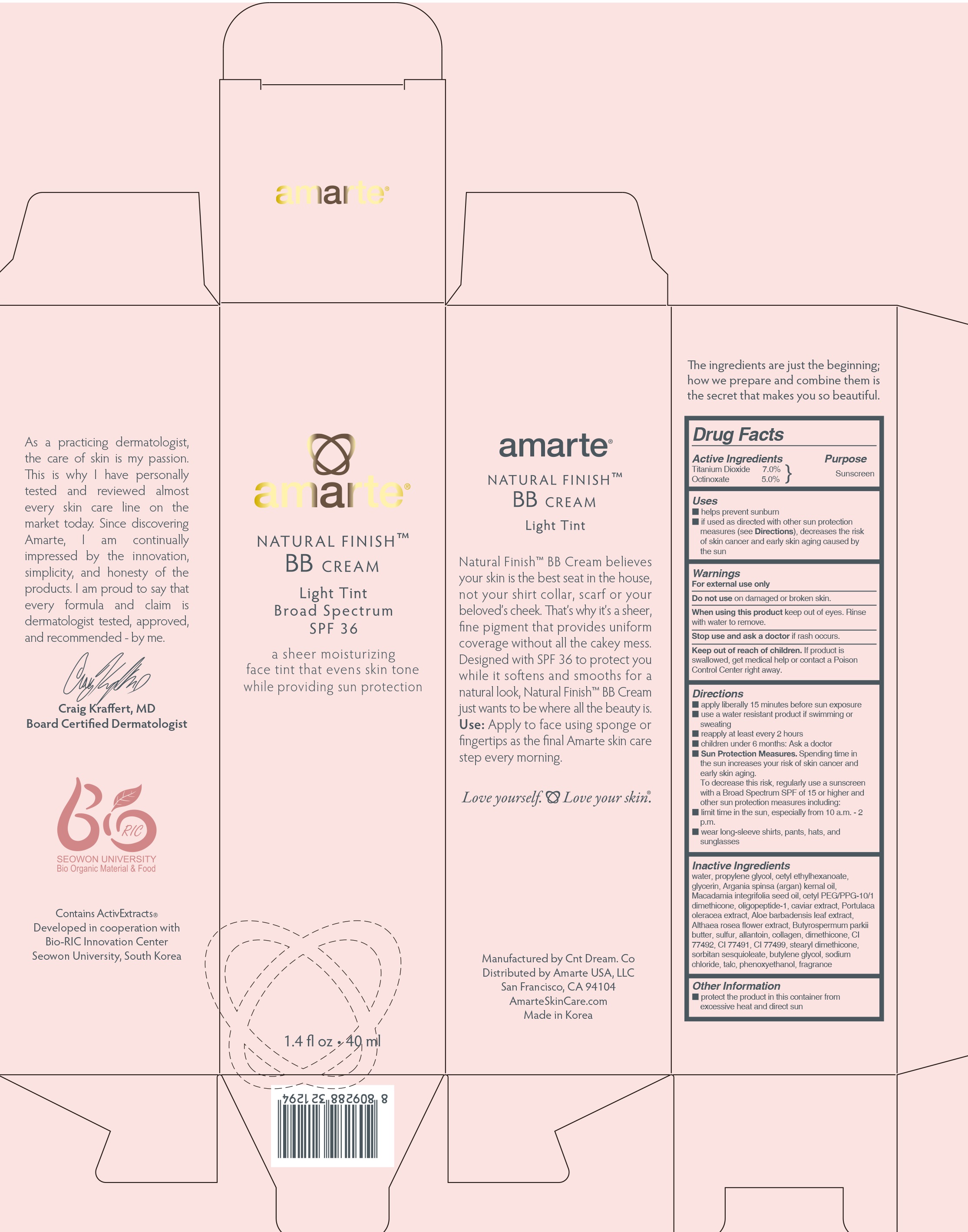 DRUG LABEL: AMARTE NATURAL FINISH BB
NDC: 69352-010 | Form: CREAM
Manufacturer: AMARTEINTERNATIONAL CO., LTD.
Category: otc | Type: HUMAN OTC DRUG LABEL
Date: 20170926

ACTIVE INGREDIENTS: Titanium Dioxide 2.8 mg/40 mL; Octinoxate 2 mg/40 mL
INACTIVE INGREDIENTS: WATER; PROPYLENE GLYCOL

ACTIVE INGREDIENT

Active Ingredients: Titanium Dioxide 7.0%, Octinoxate 5.0%

INACTIVE INGREDIENT

Inactive Ingredients:
aqua, propylene glycol, cetyl ethylhexanoate, glycerin, cetyl PEG/PPG-10/1 dimethicone, Macadamia integrifolia seed oil, Argania spinosa kernel oil, oligopeptide-1, caviar extract, portulaca oleracea extract, aloe barbadensis leaf extract, althaea rosea flower extract, butyrospermum parkii butter, sulfur, allantoin, collagen, dimethicone, CI 77492, CI 77491, CI 77499, stearyl dimethicone, sorbitan sesquioleate, butylene glycol, sodium chloride, talc, phenoxyethanol, parfum

PURPOSE

PURPOSE: SUNSCREEN

WARNINGS

For external use only
Do not use on damaged or broken skin.
When using this product keep out of eyes. Rinse with water to remove.
Stop use and ask a doctor if rash occurs.
Keep out of reach of children. If product is swallowed, get medical help or contact a Poison Control Center right away.

Keep out of reach of children. If product is swallowed, get medical help or contact a Poison Control Center right away.

Uses

- helps prevent sunburn
- if used as directed with other sun protection measures (see Directions), decreases the risk of skin cancer and early skin aging caused by the sun

Directions

- apply liberally 15 minutes before sun exposure
- use a water resistant product if swimming or sweating
- reapply at least every 2 hours
- children under 6 months: Ask a doctor
- Sun Protection Measures. Spending time in the sun increases your risk of skin cancer and early skin aging. To decrease this risk, regularly use a sunscreen with a Broad Spectrum SPF of 15 or higher and other sun protection measures including:
limit time in the sun, especially from 10 a.m. - 2 p.m.
wear long-sleeve shirts, pants, hats, and sunglasses